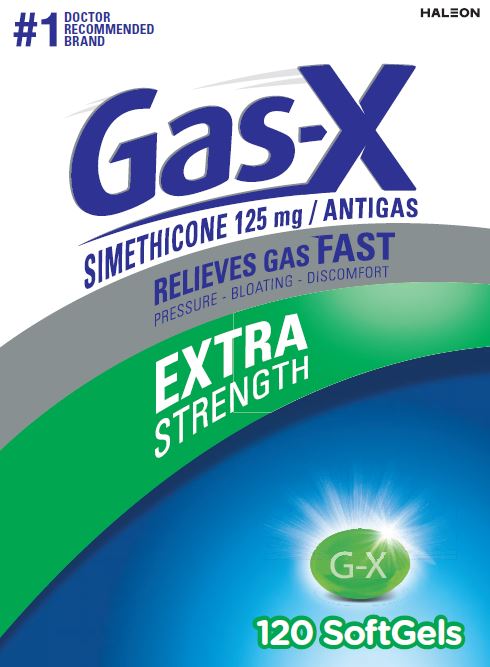 DRUG LABEL: Gas-X
NDC: 0067-6275 | Form: CAPSULE, LIQUID FILLED
Manufacturer: Haleon US Holdings LLC
Category: otc | Type: HUMAN OTC DRUG LABEL
Date: 20250314

ACTIVE INGREDIENTS: DIMETHICONE, UNSPECIFIED 125 mg/1 1
INACTIVE INGREDIENTS: D&C YELLOW NO. 10; FD&C BLUE NO. 1; FD&C RED NO. 40; GELATIN, UNSPECIFIED; GLYCERIN; HYPROMELLOSE, UNSPECIFIED; MANNITOL; MEDIUM-CHAIN TRIGLYCERIDES; PEPPERMINT OIL; PROPYLENE GLYCOL; WATER; SORBITOL; SOYBEAN LECITHIN; TITANIUM DIOXIDE

Drug Facts

Active ingredient (in each softgel)

Simethicone 125 mg

Purpose

Antigas

Use

for the relief of

- pressure, bloating, and fullness commonly referred to as gas

Directions

- adults and children 12 years and older: swallow with water 1 or 2 softgels as needed after meals and at bedtime
- do not exceed 4 softgels in 24 hours except under the advice and supervision of a physician

Other information

- store at controlled room temperature 20-25ºC (68-77ºF)
- protect from light, heat and moisture

Inactive ingredients

D&C yellow no. 10, FD&C blue no. 1, FD&C red no. 40, gelatin, glycerin, hypromellose, mannitol, medium-chain triglycerides, peppermint oil, propylene glycol, purified water, sorbitol, soy lecithin, titanium dioxide

Questions or comments?

1-800-452-0051

Additional information

Gas-XExtra Strength Softgels offer fast, effective relief of pressure and bloating that antacids can’t provide. They are specially formulated with simethicone, the antigas medicine doctors recommend most for pressure, bloating, or discomfort referred to as gas.

READ ALL PRODUCT INFORMATION BEFORE USING.

KEEP CARTON FOR IMPORTANT INFORMATION.

Gas-XExtra Strength Softgels are concentrated to contain liquid gas-fighting medicine in a small softgels so they are easy to swallow, and there is no chalky taste.

TAMPER EVIDENT FEATURE:

Do not use if blister is broken or damaged.

1-800-452-0051

Principal Display Panel

#1 DOCTOR RECOMMENDED BRAND

Gas-X

SIMETHICONE 125 mg / ANTIGAS

RELIEVES GAS FAST

PRESSURE – BLOATING – DISCOMFORT

EXTRA STRENGTH

120 SoftGels